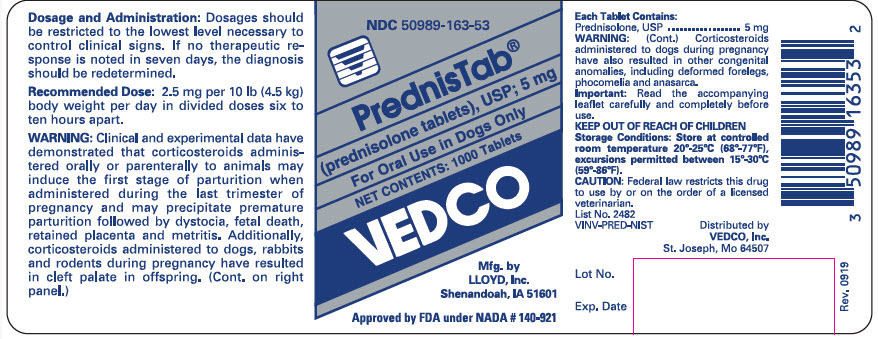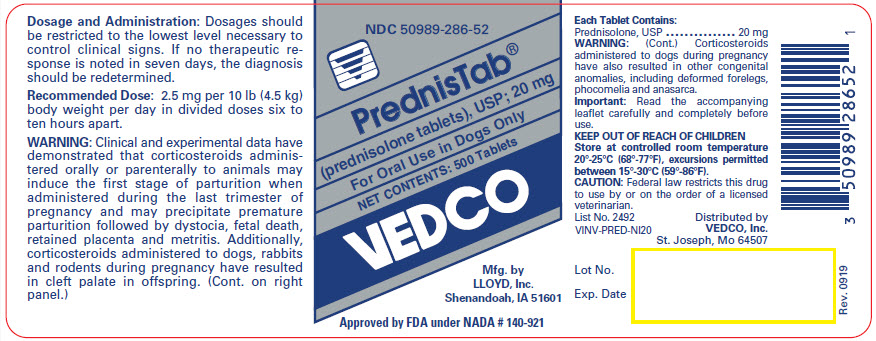 DRUG LABEL: PrednisTab
NDC: 50989-163 | Form: TABLET
Manufacturer: Vedco Inc.
Category: animal | Type: PRESCRIPTION ANIMAL DRUG LABEL
Date: 20241017

ACTIVE INGREDIENTS: PREDNISOLONE 5 mg/1 1

PrednisTab®
(Prednisolone, USP)

(prednisolone tablets), USP

For Oral Use in Dogs Only

CAUTION

Federal law restricts this drug to use by or on the order of a licensed veterinarian.

DESCRIPTION

Prednisolone, like methylprednisolone, is a potent anti-inflammatory steroid. Prednisolone, 11,17,21-trihydroxypregna-1,4-diene-3,20-dione, is a synthetic dehydrogenated analogue of cortisone. Prednisolone and methylprednisolone have a greater anti-inflammatory potency and less tendency to induce sodium and water retention than the older corticoids, cortisone and hydrocortisone. The relative anti-inflammatory potency for hydrocortisone is 1.0; cortisone is 0.8; prednisolone is 4 and methylprednisolone is 5. The relative sodium retaining potency for hydrocortisone is 4; prednisolone is 3 and methylprednisolone is 2.^1,2

INDICATIONS

PrednisTab is intended for use in dogs. The indications for PrednisTab are the same as those for other anti-inflammatory steroids and comprise the various collagen, dermal, allergic, ocular, otic, and musculoskeletal conditions known to be responsive to the anti-inflammatory corticosteroids. Representative of the conditions in which the use of steroid therapy and the benefits to be derived therefrom have had repeated confirmation in the veterinary literature are: (1) dermal conditions, such as nonspecific eczema, summer dermatitis, and burns; (2) allergic manifestations, such as acute urticaria, allergic dermatitis, drug and serum reactions, bronchial asthma, and pollen sensitivities; (3) ocular conditions, such as iritis, iridocyclitis, secondary glaucoma, uveitis, and chorioretinitis; (4) otic conditions, such as otitis externa; (5) musculoskeletal conditions, such as myositis, rheumatoid arthritis, osteoarthritis, and bursitis; (6) various chronic or recurrent diseases of unknown etiology such as ulcerative colitis and nephrosis.

In acute adrenal insufficiency, prednisolone may be effective because of its ability to correct the defect in carbohydrate metabolism and relieve the impaired diuretic response to water, characteristic of primary or secondary adrenal insufficiency. However, because this agent lacks significant mineralocorticoid activity, hydrocortisone sodium succinate, hydrocortisone, or cortisone should be used when salt retention is indicated.

CONTRAINDICATIONS

Do not use in viral infections. Prednisolone, like methylprednisolone, is contraindicated in animals with peptic ulcer, corneal ulcer, and Cushingoid syndrome. The presence of diabetes, osteoporosis, predisposition to thrombophlebitis, hypertension, congestive heart failure, renal insufficiency, and active tuberculosis necessitates carefully controlled use. Some of the above conditions occur only rarely in dogs but should be kept in mind.

CAUTION

Because of its inhibitory effect on fibroplasia, prednisolone may mask the signs of infection and enhance dissemination of the infecting organism. Hence, all animal patients receiving prednisolone should be watched for evidence of intercurrent infection. Should infection occur, it must be brought under control by use of appropriate antibacterial measures, or administration of prednisolone should be discontinued.

Warning

Not for human use. Clinical and experimental data have demonstrated that corticosteroids administered orally or by injection to animals may induce the first stage of parturition if used during the last trimester of pregnancy and may precipitate premature parturition followed by dystocia, fetal death, retained placenta, and metritis.

Additionally, corticosteroids administered to dogs, rabbits, and rodents during pregnancy have resulted in cleft palate in offspring. Corticosteroids administered to dogs during pregnancy have also resulted in other congenital anomalies, including deformed forelegs, phocomelia, and anasarca.

PRECAUTIONS

Prednisolone, like methylprednisolone and other adrenocortical steroids, is a potent therapeutic agent influencing the biochemical behavior of most, if not all, tissues of the body. Because this anti-inflammatory steroid manifests little sodium-retaining activity, the usual early sign of cortisone or hydrocortisone overdosage (i.e., increase in body weight due to fluid retention) is not a reliable index of overdosage. Hence, recommended dose levels should not be exceeded, and all animal patients receiving prednisolone should be under close medical supervision. All precautions pertinent to the use of methylprednisolone apply to prednisolone. Moreover, the veterinarian should endeavor to keep informed of current studies of corticosteroids as they are reported in the veterinary literature.

Use of corticosteroids, depending on dose, duration and specific steroid, may result in inhibition of endogenous steroid production following drug withdrawal. In patients presently receiving or recently withdrawn from systemic corticosteroid treatments, therapy with a rapid-acting corticosteroid should be considered in unusually stressful situations.

ADVERSE REACTIONS

Prednisolone is similar to methylprednisolone in regard to kinds of side effects and metabolic alterations to be anticipated when treatment is intensive or prolonged. In animal patients with diabetes mellitus, use of prednisolone may be associated with an increase in the insulin requirement. Negative nitrogen balance may occur, particularly in animals that require protracted maintenance therapy; measures to counteract persistent nitrogen loss include a high protein intake and the administration, when indicated, of a suitable anabolic agent. Excessive loss of potassium, like excessive retention of sodium, is not likely to be induced by effective maintenance doses of prednisolone. However, these effects should be kept in mind and the usual regulatory measures employed as indicated. Ecchymotic manifestations in dogs may occur. If such reactions do occur and are serious, reduction in dose or discontinuance of prednisolone therapy may be indicated.

Side effects, such as SAP and SALT enzyme elevations, weight loss, anorexia, polydipsia and polyuria have occurred following the use of synthetic cortico-steroids in dogs. Vomiting and diarrhea (occasionally bloody) have also been observed. Cushing's syndrome in dogs has been reported in association with prolonged or repeated steroid therapy.

Since prednisolone, like methylprednisolone, suppresses endogenous adrenocortical activity, it is highly important that the animal patient receiving prednisolone be under careful observation, not only during the course of treatment but for some time after treatment is terminated. Adequate adrenocortical supportive therapy with cortisone or hydrocortisone, and including ACTH, must be employed promptly if the animal is subjected to any unusual stress such as surgery, trauma, or severe infection.

ADMINISTRATION

The keystone of satisfactory therapeutic management with PrednisTab prednisolone tablets, as with other steroid predecessors, is individualization of dosage in reference to the severity of the disease, the anticipated duration of steroid therapy, and the animal patient's threshold or tolerance for steroid excess. The prime objective of steroid therapy should be to achieve a satisfactory degree of control with a minimum effective daily dose.

The dosage recommendations are suggested average total daily doses and are intended as guides. As with other orally administered corticosteroids, the total daily dose of prednisolone should be given in equally divided doses. The initial suppressive dose level is continued until a satisfactory clinical response is obtained, a period usually of 2 to 7 days in the case of musculoskeletal diseases, allergic conditions affecting the skin or respiratory tract, and ocular inflammatory diseases. If a satisfactory response is not obtained in 7 days, reevaluation of the case to confirm the original diagnosis should be made. As soon as a satisfactory clinical response is obtained, the daily dose should be reduced gradually, either to termination of treatment in the case of acute conditions (e.g., seasonal asthma, dermatitis, acute ocular inflammations) or to the minimal effective maintenance dose level in the case of chronic conditions (e.g., rheumatoid arthritis). In chronic conditions, and in rheumatoid arthritis especially, it is important that the reduction in dosage from initial to maintenance dose levels be accomplished slowly. The maintenance dose level should be adjusted from time to time as required by fluctuation in the activity of the disease and the animal's general status. Accumulated experience has shown that the long-term benefits to be gained from continued steroid maintenance are probably greater the lower the maintenance dose level. In rheumatoid arthritis in particular, maintenance steroid therapy should be at the lowest possible level.

Important: In the therapeutic management of animal patients with chronic diseases such as rheumatoid arthritis, prednisolone should be regarded as a highly valuable adjunct, to be used in conjunction with, but not as replacement for, standard therapeutic measures.

DOSAGE

2.5 mg per 10 lb (4.5 kg) body weight per day. Average total daily oral doses for dogs as follows:

5 to 20 lb (2 to 9 kg) body weight | 1.25 to 5 mg
20 to 40 lb (9 to 18 kg) body weight | 5 to 10 mg
40 to 80 lb (18 to 36 kg) body weight | 10 to 20 mg
80 to 160 lb (36 to 73 kg) body weight | 20 to 40 mg

The total daily dose should be given in divided doses, 6 to 10 hours apart.

HOW SUPPLIED

PrednisTab is available as 5 mg compressed quarter-scored tablets in bottles of 1000 and 20 mg compressed quarter-scored tablets in bottles of 500.

STORAGE

Store at controlled room temperature 20° - 25°C (68° - 77°F), excursions permitted between 15° - 30° C (59° - 86°F)

Manufactured by
LLOYD, Inc.
Shenandoah, Iowa 51601 U.S.A.

References

1. Liddle GW. Studies of structure-function relationship of steroids. II. The 6α-methylcorticosteroids. Metab Clin Exp 1958; 7:405-415.
2. Haynes RC, Jr. Adrenocorticotropic hormone; adrenocortical steroids and their synthetic analogs; inhibitors of the synthesis and actions of adrenocortical hormones. In: Gilman AG, Goodman LS, Gilman A, eds. Pharmacological basis of therapeutics. 8th ed. Elmsford, NY: Pergamon Press, 1990; 1431-1462.

Rev. 1119

Approved by FDA under NADA # 140-921

PRINCIPAL DISPLAY PANEL - 5 mg Tablet Bottle Label

NDC 50989-163-53

PrednisTab®

(prednisolone tablets), USP; 5 mg

For Oral Use in Dogs Only

NET CONTENTS: 1000 Tablets

VEDCO

Mfg. by
LLOYD, Inc.
Shenandoah, IA 51601

Approved by FDA under NADA # 140-921

PRINCIPAL DISPLAY PANEL - 20 mg Tablet Bottle Label

NDC 50989-286-52

PrednisTab®

(prednisolone tablets), USP; 20 mg

For Oral Use in Dogs Only

NET CONTENTS: 500 Tablets

VEDCO

Mfg. by
LLOYD, Inc.
Shenandoah, IA 51601

Approved by FDA under NADA # 140-921